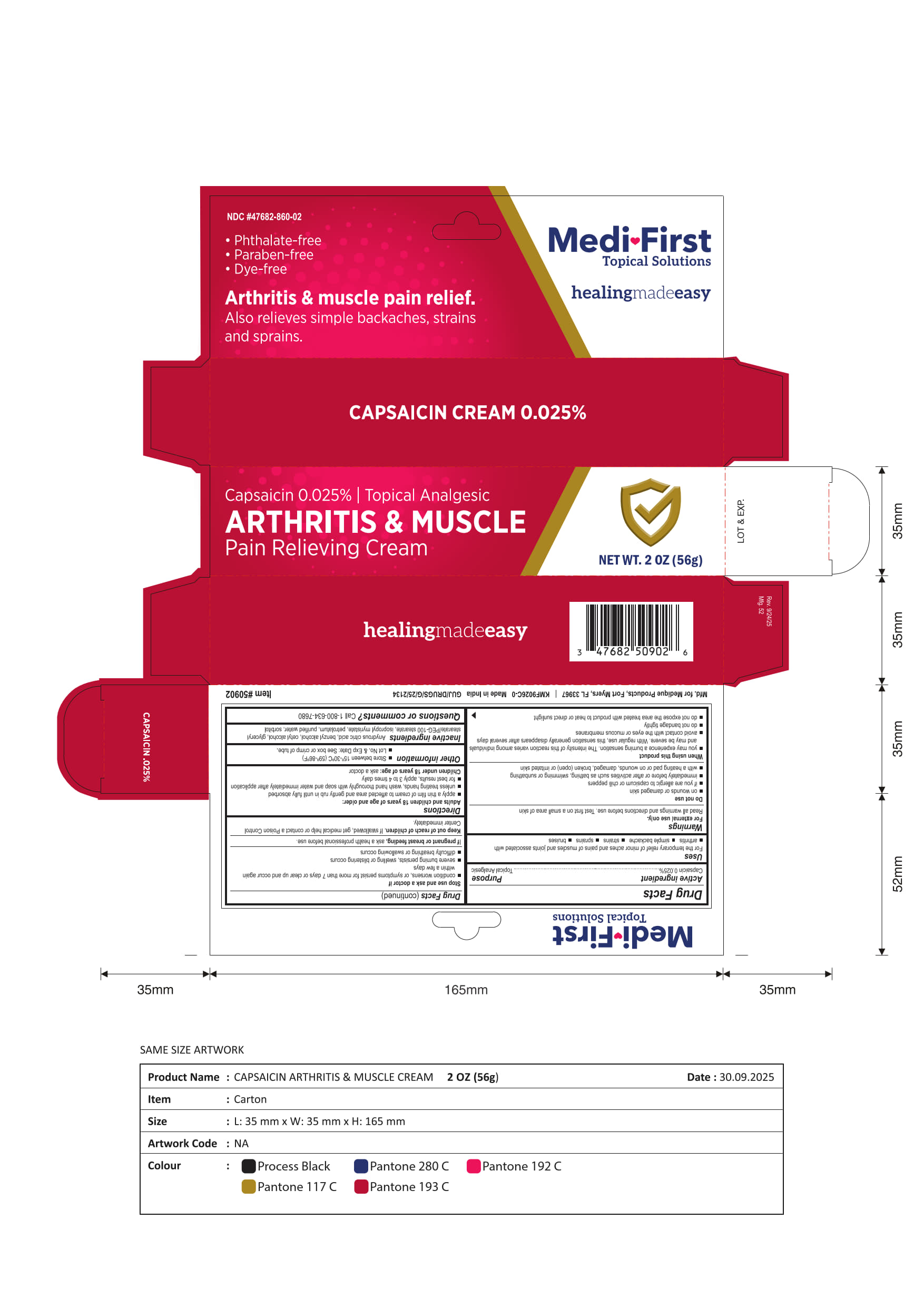 DRUG LABEL: Medi-First Capsaicin Cream
NDC: 47682-860 | Form: CREAM
Manufacturer: Unifirst First Aid Corporation
Category: otc | Type: HUMAN OTC DRUG LABEL
Date: 20260203

ACTIVE INGREDIENTS: CAPSAICIN 0.0002 g/1 g
INACTIVE INGREDIENTS: SORBITOL; ANHYDROUS CITRIC ACID; PETROLATUM; ISOPROPYL MYRISTATE; BENZYL ALCOHOL; CETYL ALCOHOL; GLYCERYL STEARATE/PEG-100 STEARATE

Medi ♥ First Capsaicin Cream 0.025%

Drug Facts

Active Ingredient

Capsaicin 0.025%

Purpose

Skin Protectant

Uses

For the temporay relief of minor aches and pains of muscles and joints assocaited with

- arthritis
- simple backache
- strains
- sprains
- bruises

Warnings

For external use only.

Read all warnings and directiosn before use. Test first on a small areaa of skin

Do not use

- on wounds or damaged skin
- if you are allergic to capsicum or chili peppers
- immediately before or after activites such as bathing, swimming or sunbathing
- with a heating pad or on wounds, damaged (open) or irritated skin

When using this product

- you may experience a burning sensation. The intesity of this reaction varies amoung individuals and may be severe. With regular use, this sensation generally disappears after several days
- avoid contact with the eyes or mucous membrames
- do not bandage tighty
- do not expose the area treated with product to heat or direct sunlight

Stop use and ask a doctor if

- condition worsens or symptoms persist for more than 7 days or clear up and occur again within a few days
- severe burning persists, swelling or blistering occurs
- difficulty breathing or swallowing occurs

If pregnant or breast feeding

If pregant or breast feeding, ask a health professional before use.

Keep our of reach of children

Keep out of reach of children.

If swallowed, get medical help or contact a Poison Control Center immediately.

Directions

Adults and children 18 years of age and older:

- apply a thin film of cream to affected area and gently rub in until fully absorbed
- unless treating hands, wash hand thoroughly with soap and water immediately after application
- for best results, apply 3 to 4 times dailu

Children under 18 years of age: ask a doctor

Other information

- Store between 15°-30° *(59°-86°F)
- Lot No. & Exp Date: See box or crimp of tube

Inactive ingredients

Anhydrous citric acid, benzyl alcohol, cetyl alcohol, glyceryl stearate/PEG-100 stearate, isopropyl myristate, petrolatum, purified water, sorbitol

Questions or comments? Call 1-800-634-7680

Principal Display Panel

Medi ♥ First

Topical Solutions

healingmade easy

- Phthalate-free
- Paraban-free
- Dye-free

Arthritis & muscle pain relief.

Also relieves simple backaches, strains

and sprains.